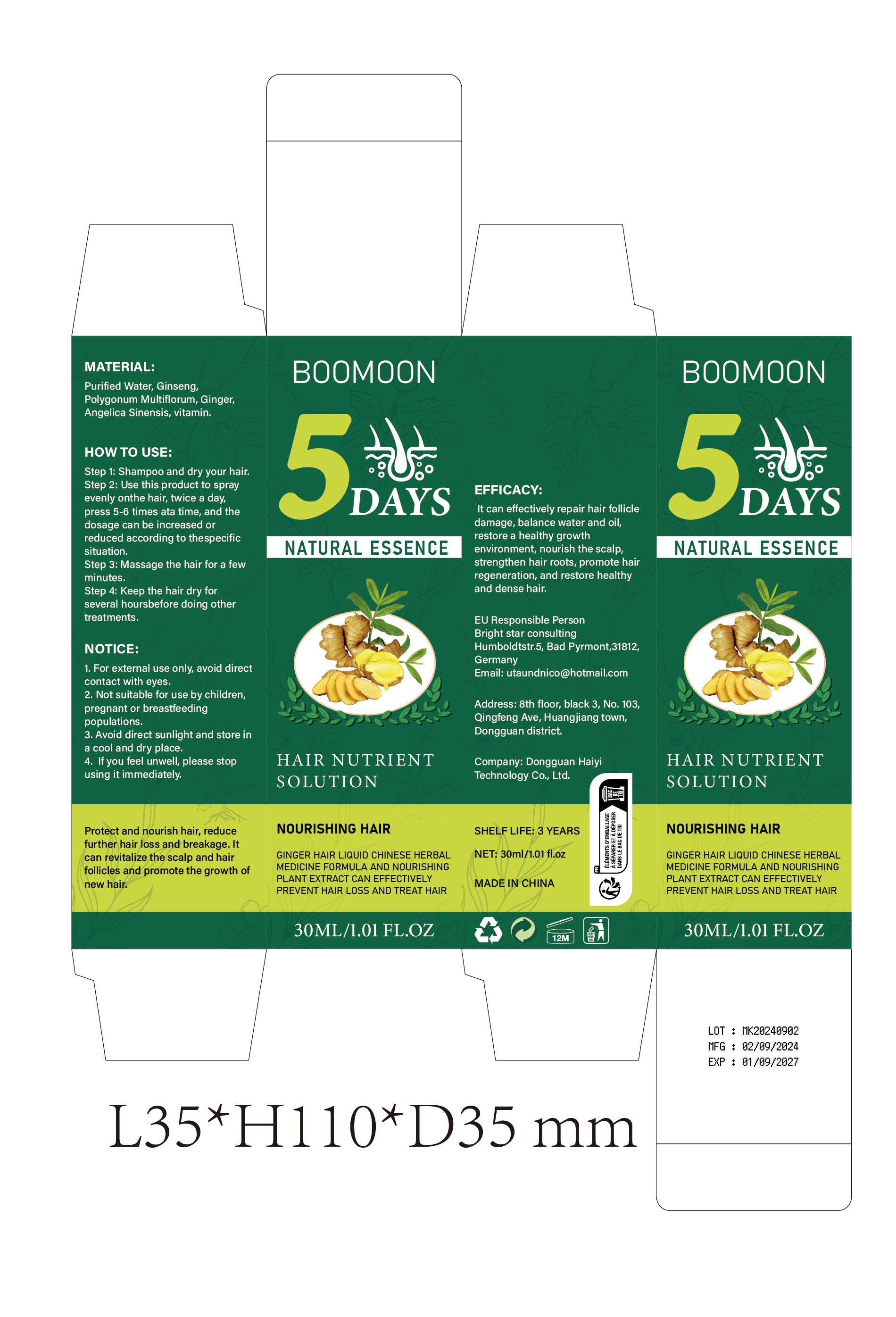 DRUG LABEL: NOURISHING HAIR
NDC: 84732-011 | Form: LIQUID
Manufacturer: Dongguan Haiyi Technology Co.,Ltd.
Category: otc | Type: HUMAN OTC DRUG LABEL
Date: 20240925

ACTIVE INGREDIENTS: WATER 1 mg/30 mL
INACTIVE INGREDIENTS: POLYGONUM CUSPIDATUM LEAF; GINGER; VITAMIN D; PANAX GINSENG WHOLE; ANGELICA SINENSIS ROOT OIL

ACTIVE INGREDIENT

Purified Water

Inactive ingredient

Ginseng,Polygonum Multiflorum, Ginger ，Angelica Sinensis, vitamin.

Purpose section

It can effectively repair hair follicle damage, balance water and oil,restore a healthy growth environment, nourish the scalp strengthen hair roots, promote hair regeneration, and restore healthy and dense hair.

Warning

1. For external use only avoid directcontact with eyes.

2. Not suitable for use by children,pregnant or breastfeedingpopulations.

3. Avoid direct sunlight and store ina cool and dry place.

4. lf you feel unwell, please stopusing it immediately.

stop use

This product may cause allergic reactions in asmall number of people.
lf youexperience any discomfort,please stop using it immediately.

not use

Not suitable for use by children, pregnantor breastfeeding people.

OUT OF CHILDREN

KEEP THE PRODUCT OUT OF REACH OF CHILDREN to

HOW TO USE

Step 1: Shampoo and dry your hair.

Step 2: Use this product to sprayevenly onthe hair, twice a daypress 5-6 times ata time, and thedosage can be increased orreduced according to thespecificsituation.

Step 3: Massage the hair for a fewminutes.

Step 4: Keep the hair dry forseveral hoursbefore doing othertreatments

Dosage

take an appropriateamount,Use 2-3 times a week